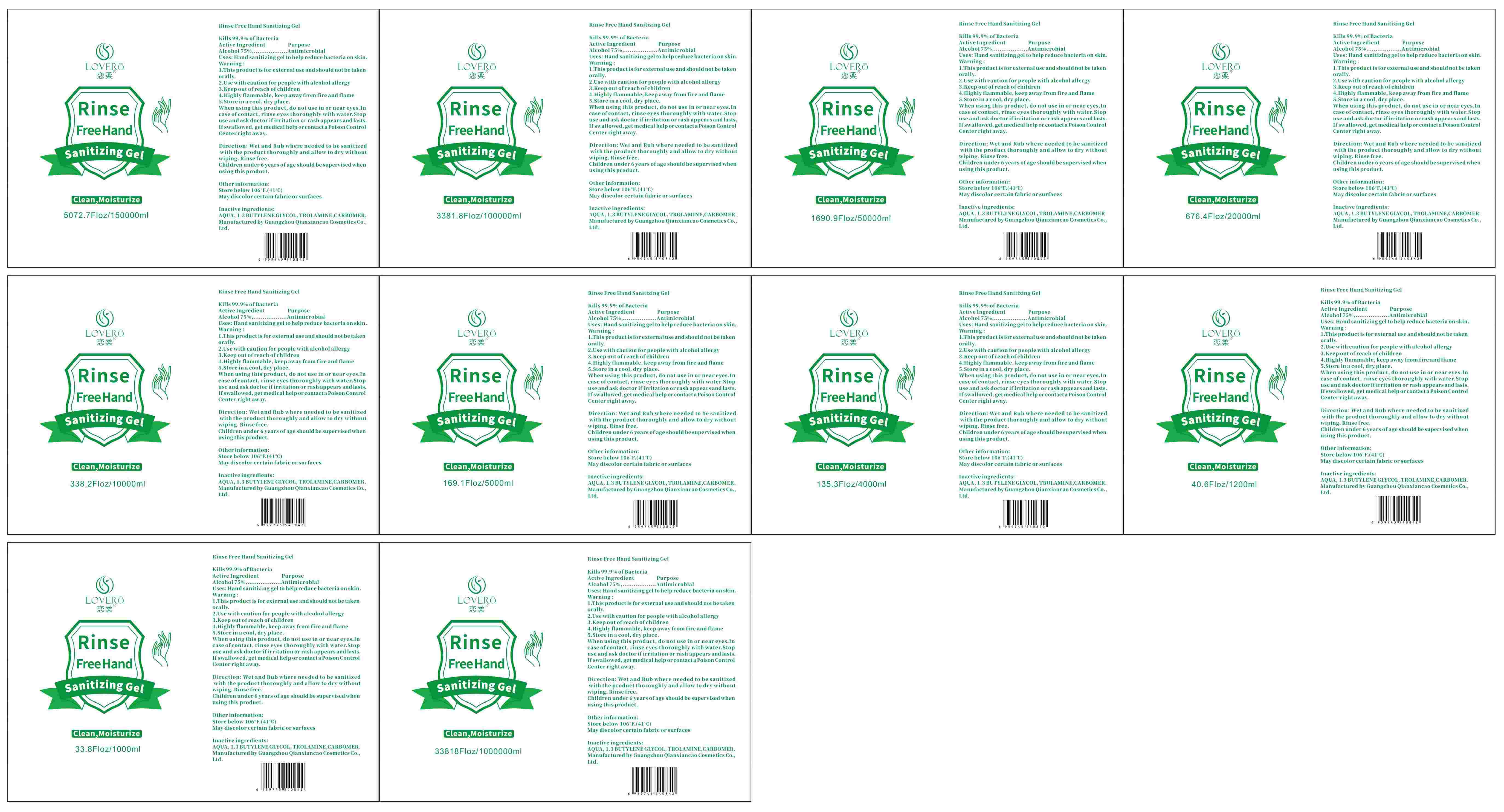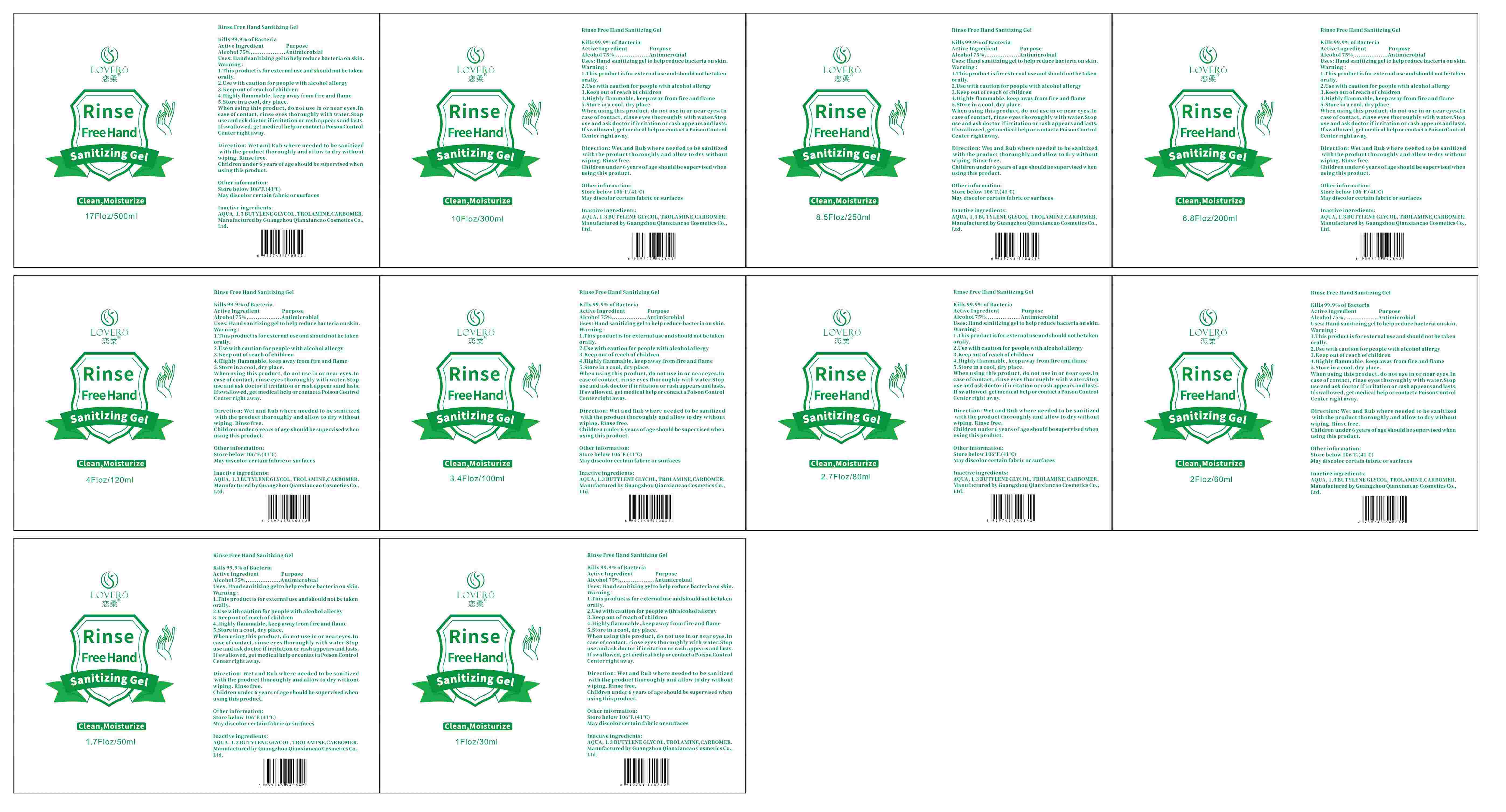 DRUG LABEL: Rinse Free Hand Sanitizing Gel
NDC: 78963-005 | Form: GEL
Manufacturer: Guangzhou Qianxiancao Cosmetics Co.,Ltd.
Category: otc | Type: HUMAN OTC DRUG LABEL
Date: 20200729

ACTIVE INGREDIENTS: ALCOHOL 75 mL/100 mL
INACTIVE INGREDIENTS: BUTYLENE GLYCOL; TROLAMINE; WATER; CARBOMER HOMOPOLYMER, UNSPECIFIED TYPE

Active Ingredient(s)

Alcohol 75% v/v. Purpose: Antiseptic

Purpose

Antiseptic, Hand Sanitizer

Use

Hand sanitizinggel to help reduce bacteria on skin.

Warnings

WarningI This product is for external use and should not be takenorally

2. Use with caution for people with alcohol allergy

3. Keep out of reach of children

4. Highly flammable, keep away from fire and flame

5. Store in a cool, dry placeWhen using this produet, do not use in or near eyes. Incase of contact, rinse eyes thoroughly with water. Stopuse and ask doctor if irritation or rash appears and lastsIf swallowed, get medical help or contact a Poison ControlCenter right away

Do not use

/

when using this product, do not use in or near eyes. Incase of contact, rinse eyes thoroughly with water. Stopuse and ask doctor if irritation or rash appears and lastsIf swallowed, get medical help or contact a Poison ControlCenter right away.

Stop use and ask a doctor if irritation or rash occurs. These may be signs of a serious condition.

Keep out of reach of children. If swallowed, get medical help or contact a Poison Control Center right away.

Directions

Direction: Wet and Rub where needed to be sanitizedwith the product thoroughly and allow to dry withoutwiping.

Rinse free.Children under 6 years of age should be supervised whenusing this product.

Other information

- Other information:Store below 106F(41 C)May discolor certain fabric or surfaces

Inactive ingredients

AQUA, 1.3 BUTYLENE GLYCOL, TROLAMINE, CARBOMER.